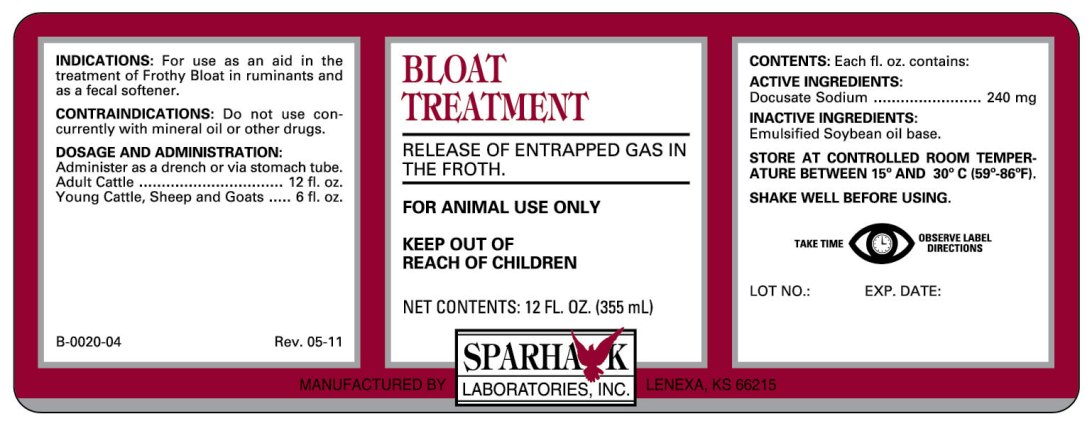 DRUG LABEL: BLOAT TREATMENT
NDC: 58005-378 | Form: EMULSION
Manufacturer: Sparhawk Laboratories, Inc.
Category: animal | Type: OTC ANIMAL DRUG LABEL
Date: 20180329

ACTIVE INGREDIENTS: DOCUSATE SODIUM 240 mg/29.57 mL

BLOAT TREATMENT

INDICATIONS AND USAGE

RELEASE OF ENTRAPPED GAS IN THE FROTH

FOR ANIMAL USE ONLY

KEEP OUT OF REACH OF CHILDREN

INDICATIONS

For use as an aid in the treatment of Frothy Bloat in ruminants and as a fecal softener.

CONTRAINDICATIONS

Do not use concurrently with mineral oil or other drugs.

DOSAGE AND ADMINISTRATION

Administer as a drench or via stomach tube.
Adult Cattle................................. 12 fl. oz.
Young Cattle, Sheep and Goats ..... 6 fl. oz.

CONTENTS

Each fl. oz. contains:

ACTIVE INGREDIENTS:
Docusate Sodium ................. 240 mg

INACTIVE INGREDIENTS:
Emulsified Soybean oil base.

STORAGE AND HANDLING

STORE AT CONTROLLED ROOM TEMPERATURE BETWEEN 15o AND 30o C (59o-86oF).

SHAKE WELL BEFORE USING

TAKE TIME OBSERVE LABEL DIRECTIONS